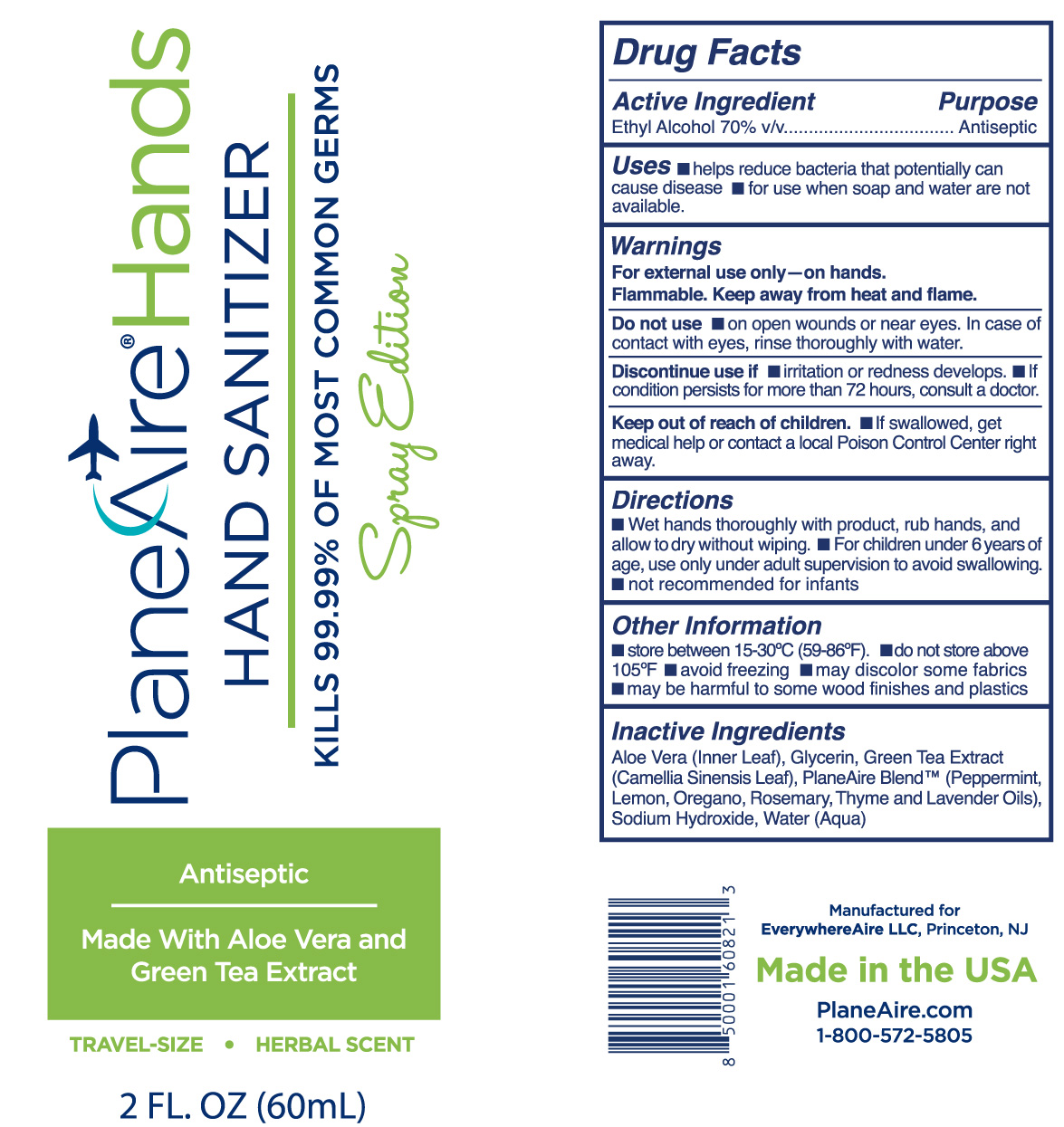 DRUG LABEL: PlaneAire Hands hand sanitizer
NDC: 80335-105 | Form: SPRAY
Manufacturer: EverywhereAire LLC
Category: otc | Type: HUMAN OTC DRUG LABEL
Date: 20231220

ACTIVE INGREDIENTS: ALCOHOL 70 mL/100 mL
INACTIVE INGREDIENTS: ALOE VERA LEAF POLYSACCHARIDES; GLYCERIN; LEMON OIL; THYME OIL; ROSEMARY OIL; GREEN TEA LEAF; LAVENDER OIL; OREGANO LEAF OIL; CARBOMER 980; WATER; PEPPERMINT OIL

PlaneAire Hands spray Hand Sanitizer Signature Herbal

The hand sanitizer is manufactured using only the following United States Pharmacopoeia (USP) grade ingredients in the preparation of the product (percentage in final product formulation) consistent with World Health Organization (WHO) recommendations:

1. Alcohol (ethanol) (USP or Food Chemical Codex (FCC) grade) (70%, volume/volume (v/v)) in an aqueous solution denatured according to Alcohol and Tobacco Tax and Trade Bureau regulations in 27 CFR part 20.
2. Glycerol.
3. Sodium hydroxide
4. Water.
5. other Inactive ingredients

Active Ingredient(s)

Alcohol 70% v/v.

Purpose

Antiseptic, Hand Sanitizer

Use

Hand Sanitizer to help reduce bacteria that potentially can cause disease. For use when soap and water are not available.

Warnings

For external use only- on hands. Flammable. Keep away from heat or flame

Do not use

- on open skin wounds or near eyes. In case of contact with eyes, rinse thoroughly with water

When using this product keep out of eyes, ears, and mouth. In case of contact with eyes, rinse eyes thoroughly with water.
Stop use and ask a doctor if irritation or rash occurs. These may be signs of a serious condition.
Keep out of reach of children. If swallowed, get medical help or contact a Poison Control Center right away.

Stop use if irritation or redness develops. If condition persists for more than 72 hours, consult a doctor.

Keep out of reach of children. If swallowed, get medical help or contact a Poison Control Center right away.

Directions

- Wet hands thoroughly with product, rub hands, and allow to dry without wiping.
- For children under 6 years of age, use only under adult supervision to avoid swallowing.
- not recommended for infants

Dosage and Administration

Wet hands thoroughly with product, rub hands, and allow to dry without wiping.
For children under 6 years of age, use only under adult supervision to avoid swallowing.
not recommended for infants

Other information

- store between 15-30C (59-86F)
- do not store above 105F
- Avoid freezing
- may discolor some fabrics
- may be harmful to some wood finishes and plastics

Inactive ingredients

aloe inner leaf, green tea extract, glycerin, Carbomer, lavender oil, lemon oil, oregano oil, peppermint oil, rosemary oil, thyme oil, water

Package Label - Principal Display Panel

60 mL NDC: 80335-105-02